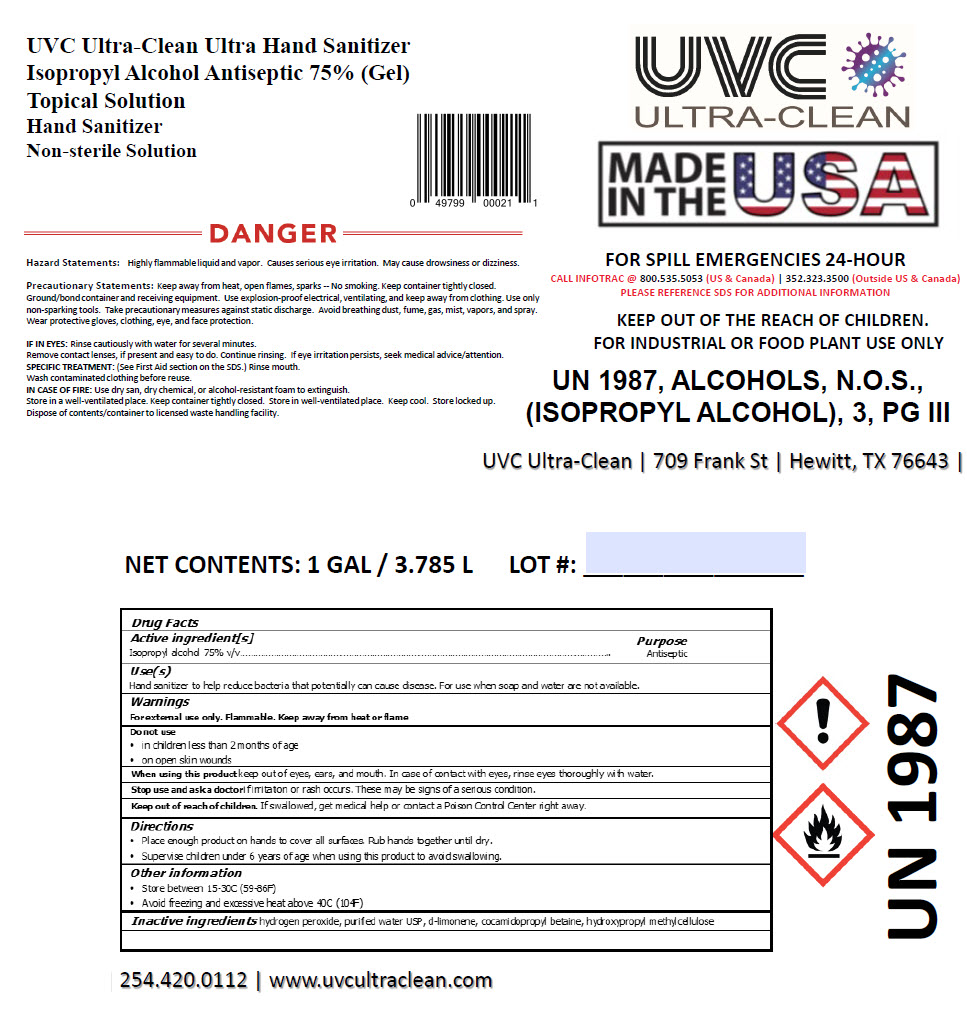 DRUG LABEL: UVC Ultra-Clean Ultra Hand Sanitizer
NDC: 54555-133 | Form: LIQUID
Manufacturer: Brainerd Chemical Company Inc.,
Category: otc | Type: HUMAN OTC DRUG LABEL
Date: 20200814

ACTIVE INGREDIENTS: Isopropyl Alcohol 750 mL/1 L
INACTIVE INGREDIENTS: Cocamidopropyl Betaine; hydrogen peroxide; water; Limonene, (+)-; HYDROXYMETHYL CELLULOSE

UVC Ultra-Clean Ultra Hand Sanitizer

Drug Facts

Active ingredient[s]

Isopropyl alcohol 75% v/v

Purpose

Antiseptic

Use(s)

Hand sanitizer to help reduce bacteria that potentially can cause disease. For use when soap and water are not available.

Warnings

For external use only. Flammable. Keep away from heat or flame

Do not use

- in children less than 2 months of age
- on open skin wounds

When using this product keep out of eyes, ears, and mouth. In case of contact with eyes, rinse eyes thoroughly with water.

Stop use and ask a doctor if irritation or rash occurs. These may be signs of a serious condition.

Keep out of reach of children. If swallowed, get medical help or contact a Poison Control Center right away.

Directions

- Place enough product on hands to cover all surfaces. Rub hands together until dry.
- Supervise children under 6 years of age when using this product to avoid swallowing.

Other information

- Store between 15-30C (59-86F)
- Avoid freezing and excessive heat above 40C (104F)

Inactive ingredients

hydrogen peroxide, purified water USP, d-limonene, cocamidopropyl betaine, hydroxypropyl methylcellulose

PRINCIPAL DISPLAY PANEL - 3.785 L Jug Label

UVC
ULTRA-CLEAN

MADE
IN THE
USA

FOR SPILL EMERGENCIES 24-HOUR
CALL INFOTRAC @ 800.535.5053 (US & Canada) | 352.323.3500 (Outside US & Canada)
PLEASE REFERENCE SDS FOR ADDITIONAL INFORMATION

KEEP OUT OF THE REACH OF CHILDREN.
FOR INDUSTRIAL OR FOOD PLANT USE ONLY

UN 1987, ALCOHOLS, N.O.S.,
(ISOPROPYL ALCOHOL), 3, PG III

UVC Ultra-Clean | 709 Frank St | Hewitt, TX 76643 | 254.420.0112 | www.uvcultraclean.com